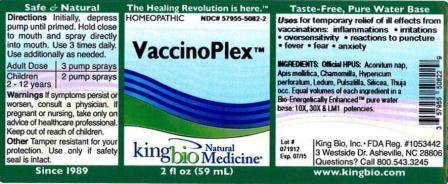 DRUG LABEL: Vaccinoplex
NDC: 57955-5082 | Form: LIQUID
Manufacturer: King Bio Inc.
Category: homeopathic | Type: HUMAN OTC DRUG LABEL
Date: 20120814

ACTIVE INGREDIENTS: APIS MELLIFERA 10 [hp_X]/59 mL; MATRICARIA RECUTITA 10 [hp_X]/59 mL; HYPERICUM PERFORATUM 10 [hp_X]/59 mL; LEDUM PALUSTRE TWIG 10 [hp_X]/59 mL; PULSATILLA VULGARIS 10 [hp_X]/59 mL; SILICON DIOXIDE 10 [hp_X]/59 mL; THUJA OCCIDENTALIS LEAFY TWIG 10 [hp_X]/59 mL
INACTIVE INGREDIENTS: WATER

VaccinoPlex

Warnings

If symptoms persist or worsen, consult a phyiscian. If pregnant or nursing, take only on advice of healthcare professional. Keep out of reach of children.

Keep out of reach of children.

Active Ingredient

Official HPUS: Aconitum napellus, Apis mellifica, Chamomilla, Hypericum perforatum, Ledum palustre, Pulsatilla, Silicea, Thuja occidentalis.

Inactive Ingredient

Equal volumes of each ingredient in a Bio-Energetically Enhanced pure water base: 10X, 30X, and LM1 potencies.

Purpose

Uses for temporary relief of ill effects from vaccinations:

- inflammations
- irritations
- oversensitivity
- reactions to puncture
- fever
- fear
- anxiety

Dosage and Administration

Directions: initially, depress pump until primed. Hold close to mouth and spray directly into mouth. Use 3 times daily. Use additionally as needed.

Adult dose 3 pump sprays

Children 2 - 12 years 2 pump sprays

Indications and usage

For temporary relief of ill effects from vaccinations: inflammations, irritations, oversensitivity, reactions to pumcture, fever, fear and anxiety.

PACKAGE LABEL

King Bio Inc.

3 Westside drive

Asheville, NC 28806

Questions? Call 800.543.3245

www.kingbio.com